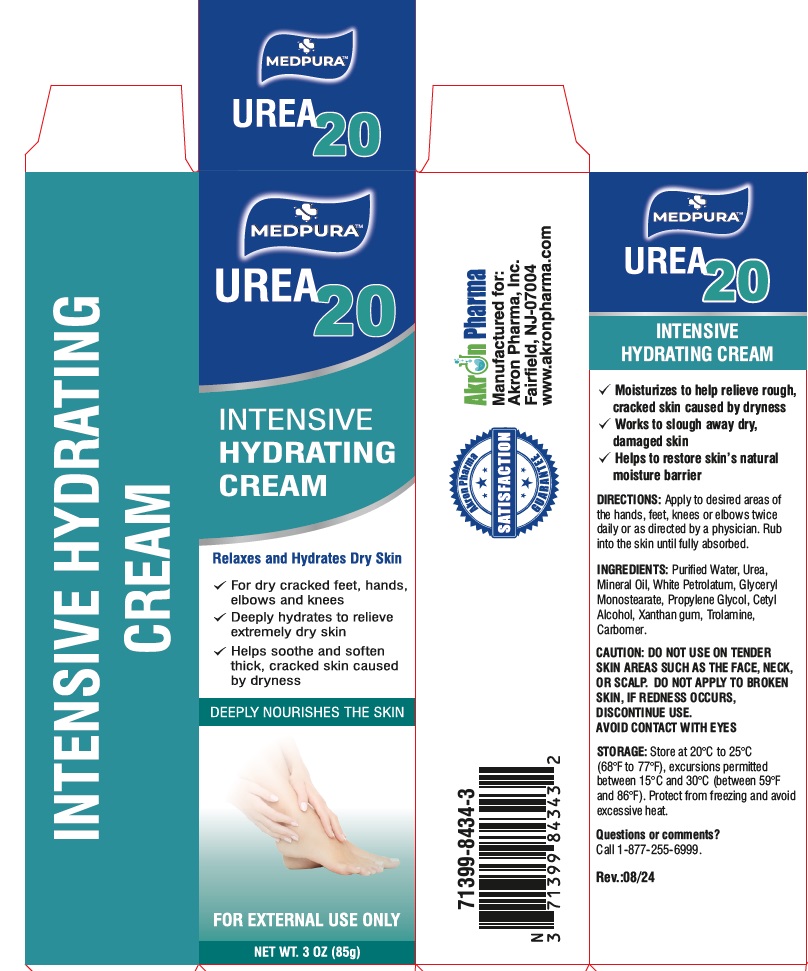 DRUG LABEL: MEDPURA Urea 20
NDC: 00371399843432
Manufacturer: AKRON PHARMA INC
Category: other | Type: COSMETIC
Date: 20250113

Urea 20
Intensive Hydrating Cream

INTENSIVE HYDRATING CREAM

- Moisturizes to help relieve rough, cracked skin caused by dryness
- Works to slough away dry, damaged skin
- Helps to restore skin’s natural moisture barrier

DIRECTIONS: Apply to desired areas of the hands, feet, knees or elbows twice daily or as directed by a physician. Rub into the skin until fully absorbed.

INGREDIENTS: Purified Water, Urea, Mineral Oil, White Petrolatum, Glyceryl Monostearate, Propylene Glycol, Cetyl Alcohol, Xanthan gum, Trolamine, Carbomer.

CAUTION: DO NOT USE ON TENDER SKIN AREAS SUCH AS THE FACE, NECK, OR SCALP. DO NOT APPLY TO BROKEN SKIN, IF REDNESS OCCURS, DISCONTINUE USE. AVOID CONTACT WITH EYES

Questions or comments?
Call 1-877-255-6999.

STORAGE: Store at 20°C to 25°C
(68°F to 77°F), excursions permitted
between 15°C and 30°C (between 59°F
and 86°F). Protect from freezing and avoid
excessive heat.

Manufactured for:

Akron Pharma, Inc.
Fairfield, NJ 07004

www.akronpharma.com